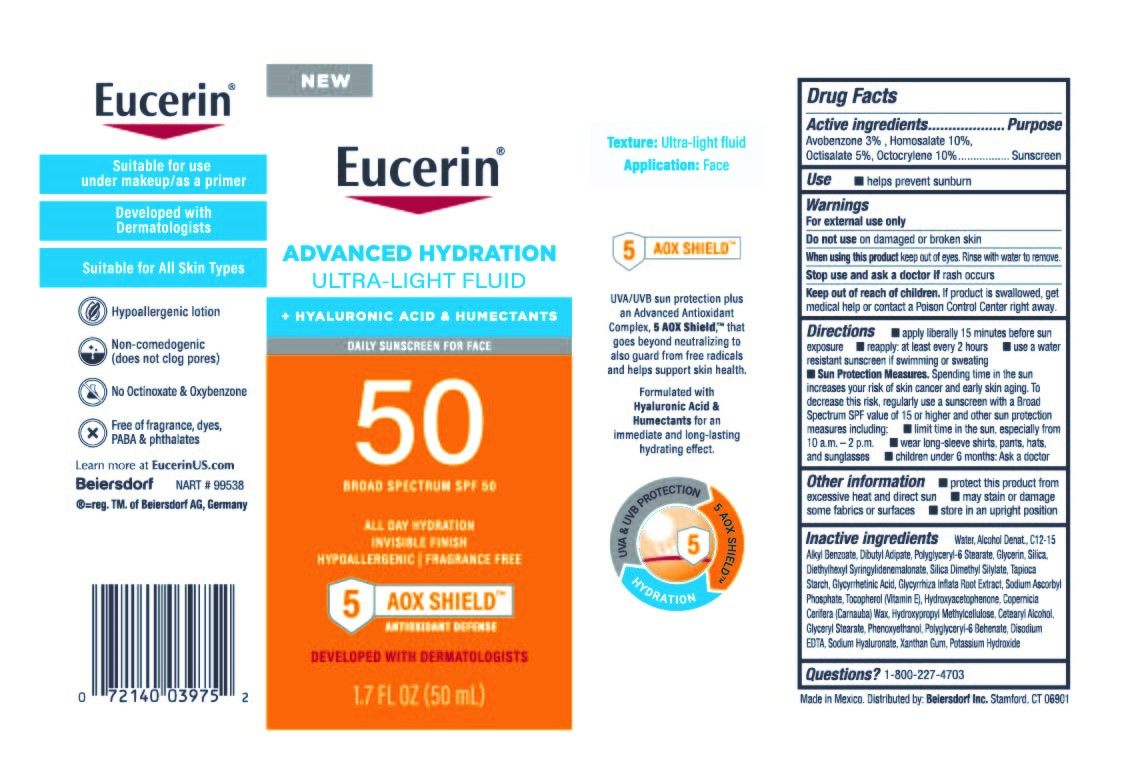 DRUG LABEL: Eucerin Advanced Hydration Ultra-Light Face Sunscreen SPF 50
NDC: 66800-0375 | Form: LOTION
Manufacturer: Beiersdorf Inc
Category: otc | Type: HUMAN OTC DRUG LABEL
Date: 20251231

ACTIVE INGREDIENTS: OCTOCRYLENE 10 g/100 g; HOMOSALATE 10 g/100 g; AVOBENZONE 3 g/100 g; OCTISALATE 5 g/100 g
INACTIVE INGREDIENTS: COPERNICIA CERIFERA (CARNAUBA) WAX; HYDROXYPROPYL METHYLCELLULOSE; C12-15 ALKYL BENZOATE; DISODIUM EDTA-COPPER; XANTHAN GUM; CALCIUM SILICATE; POTASSIUM HYDROXIDE; SILICA DIMETHYL SILYLATE; TOCOPHEROL; PHENOXYETHANOL; DIETHYLHEXYL SYRINGYLIDENEMALONATE; CETOSTEARYL ALCOHOL; POLYGLYCERYL-6 STEARATE; STARCH, TAPIOCA; SODIUM HYALURONATE; GLYCYRRHETINIC ACID; WATER; DIBUTYL ADIPATE; SODIUM ASCORBYL PHOSPHATE; HYDROXYACETOPHENONE; GLYCERYL STEARATE SE; POLYGLYCERYL-6 BEHENATE; ALCOHOL; GLYCERIN; GLYCYRRHIZA INFLATA ROOT

Eucerin Advanced Face Fluid SPF 50

Active ingredients

Avobenzone 3%, Homosalate 10%,

Octisalate 5%, Octocrylene 10%

Purpose

Sunscreen

Uses

helps prevent sunburn

Warnings

For external use only

Do not useon damaged or broken skin

WHEN USING

When using this productkeep out of eyes. Rinse with water to remove.

Stop use and ask a doctor ifrash occurs

Keep out of reach of children.If product is swallowed, get medical help or contact a Poison Control Center right away.

Directions

■ apply liberally 15 minutes before sun exposure

■ reapply:

■ at least every 2 hours

■ use a water resistant sunscreen if swimming or sweating

■ Sun Protection Measures. Spending time in the sun increases your risk of skin cancer and early skin aging. To decrease this risk, regularly use a sunscreen with a Broad Spectrum SPF value of 15 or higher and other sun protection measures including:

■ limit time in the sun, especially from 10 a.m. – 2 p.m.

■ wear long-sleeve shirts, pants, hats, and sunglasses

■ children under 6 months: Ask a doctor

Other information

■ may stain or damage some fabrics or surfaces

■ store in an upright position

Inactive ingredients

Water, Alcohol Denat., C12-15 Alkyl Benzoate, Dibutyl Adipate, Polyglyceryl-6 Stearate, Glycerin, Silica, Diethylhexyl Syringylidenemalonate, Silica Dimethyl Silylate, Tapioca Starch, Glycyrrhetinic Acid, Glycyrrhiza Inflata Root Extract, Sodium Ascorbyl Phosphate, Tocopherol (Vitamin E), Hydroxyacetophenone, Copernicia Cerifera (Carnauba) Wax, Hydroxypropyl Methylcellulose, Cetearyl Alcohol, Glyceryl Stearate, Phenoxyethanol, Polyglyceryl-6 Behenate, Disodium EDTA, Sodium Hyaluronate, Xanthan Gum, Potassium Hydroxide

Questions?

1-800-227-4703

PACKAGE LABEL

Eucerin Advanced Hydration Ultra-Light Fluid +

Hyaluronicd Acid & Humectants

Daily Sunscreen for Face

Broad Spectrum SPF 50

All Day Hydation

Invisible Finish

Hypoallergenic | Fragrance Free

5 AOX Shield

Developed with Dermatologists